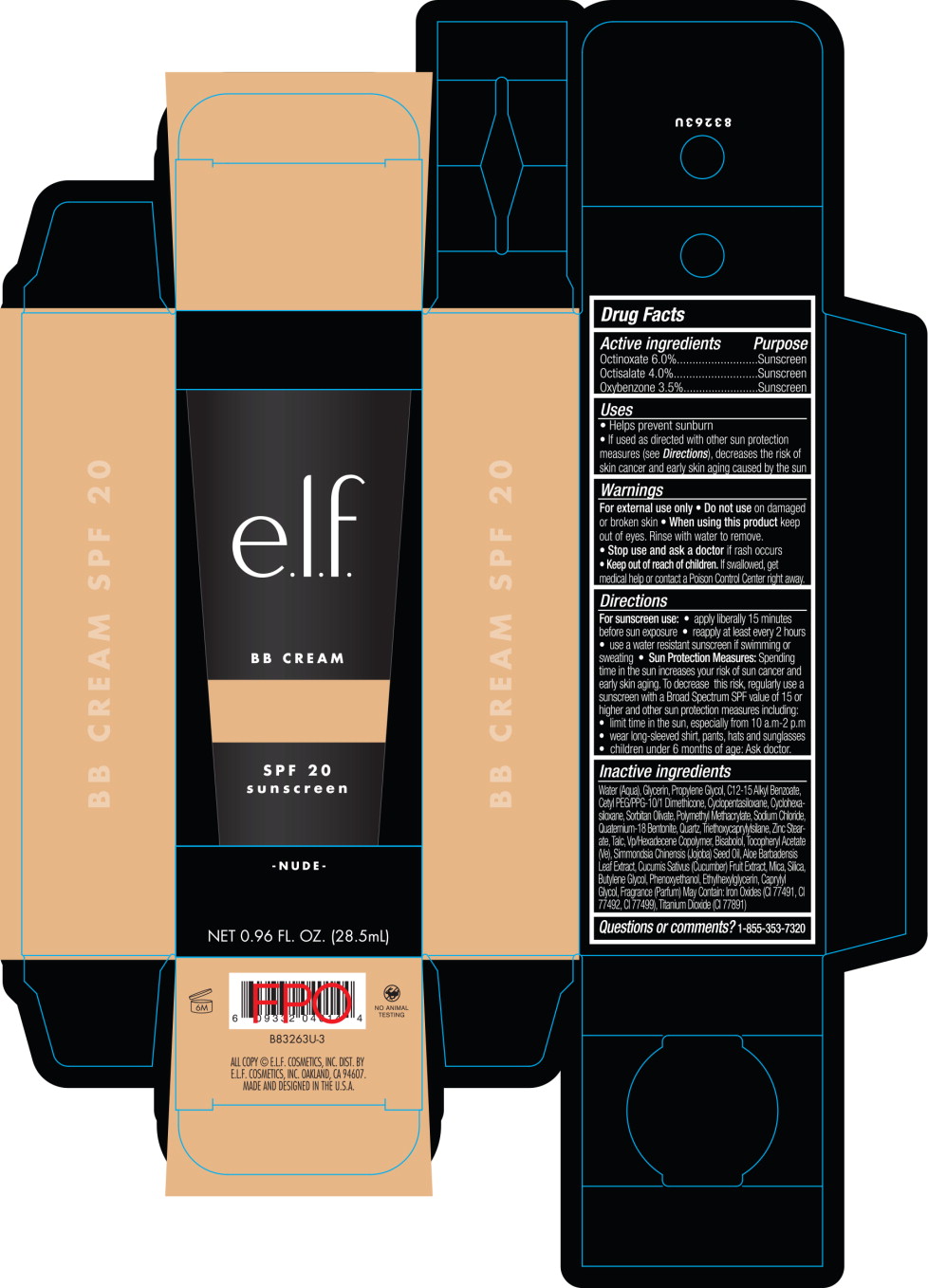 DRUG LABEL: BB Cream SPF 20 Nude
NDC: 76354-862 | Form: CREAM
Manufacturer: J. A. Cosmetics U.S. INC
Category: otc | Type: HUMAN OTC DRUG LABEL
Date: 20201217

ACTIVE INGREDIENTS: OCTINOXATE 60 mg/1 mL; OXYBENZONE 35 mg/1 mL; OCTISALATE 40 mg/1 mL
INACTIVE INGREDIENTS: WATER; SILICON DIOXIDE; MICA; GLYCERIN; PROPYLENE GLYCOL; ALKYL (C12-15) BENZOATE; FERRIC OXIDE RED; FERRIC OXIDE YELLOW; FERROSOFERRIC OXIDE; TITANIUM DIOXIDE; CETYL PEG/PPG-10/1 DIMETHICONE (HLB 2); SORBITAN OLIVATE; SODIUM CHLORIDE; BENTOQUATAM; TRIETHOXYCAPRYLYLSILANE; ZINC STEARATE; TALC; .ALPHA.-TOCOPHEROL ACETATE; ALOE VERA LEAF; JOJOBA OIL; CUCUMBER; PHENOXYETHANOL; ETHYLHEXYLGLYCERIN; CYCLOMETHICONE 5; BUTYLENE GLYCOL; CAPRYLYL GLYCOL; CYCLOMETHICONE 6; POLY(METHYL METHACRYLATE; 450000 MW); LEVOMENOL; VINYLPYRROLIDONE/HEXADECENE COPOLYMER

BB Cream SPF 20 Nude

Active ingredients

Octinoxate 6.0%

Octisalate 4.0%

Oxybenzone 3.5%

Purpose

Sunscreen

Uses

- Helps prevent sunburn
- If used as directed with other sun protection measures (see Directions), decreases the risk of skin cancer and early skin aging caused by the sun

Warnings

For external use only

Do not use

on damaged or broken skin

When using this product

keep out of eyes. Rinse with water to remove.

Stop use and ask a doctor

if rash occurs

Keep out of reach of children.

If swallowed, get medical help or contact a Poison Control Center right away.

Directions

For sunscreen use:

- apply liberally 15 minutes before sun exposure
- reapply at least every 2 hours
- use a water resistant sunscreen if swimming or sweating
- Sun Protection Measures: Spending time in the sun increases your risk of sun cancer and early skin aging. To decrease this risk, regularly use a sunscreen with a Broad Spectrum SPF value of 15 or higher and other sun protection measures including:
  - limit time in the sun, especially from 10 a.m-2 p.m
  - wear long-sleeved shirt, pants, hats and sunglasses
  - children under 6 months of age: Ask doctor.

Inactive ingredients

Water (Aqua), Glycerin, Propylene Glycol, C12-15 Alkyl Benzoate, Cetyl PEG/PPG-10/1 Dimethicone, Cydopentasiloxane, Cyclohexasiloxane, Sorbitan Olivate, Polymethyl Methacrylate, Sodium Chloride, Quatemium-18 Bentonite, Quartz, Triethoxycaprylylsilane, Zinc Stearate, Talc, Vp/Hexadecene Copolymer, Bisabolol, Tocopheryl Acetate (Ve), Simmondsia Chinensis (Jojoba) Seed Oil, Aloe Barbadensis Leat Extract, Cucumis Sativus (Cucumber) Fruit Extract, Mica, Silica, Butylene Glycol, Phenoxyethanol, Ethylhexylglycerin, Caprylyl Glycol, Fragrance (Parfum) May Contain: Iron Oxides (Cl 77491, Cl 77492, Cl 77499), Titanium Dioxide (Cl 77891)

Questions or comments?

1-855-353-7320

Principal Display Panel - 28.5 mL Carton Label

e.l.f.

BB CREAM

SPF 20
sunscreen

NUDE

NET 0.96 FL. OZ. (28.5mL)